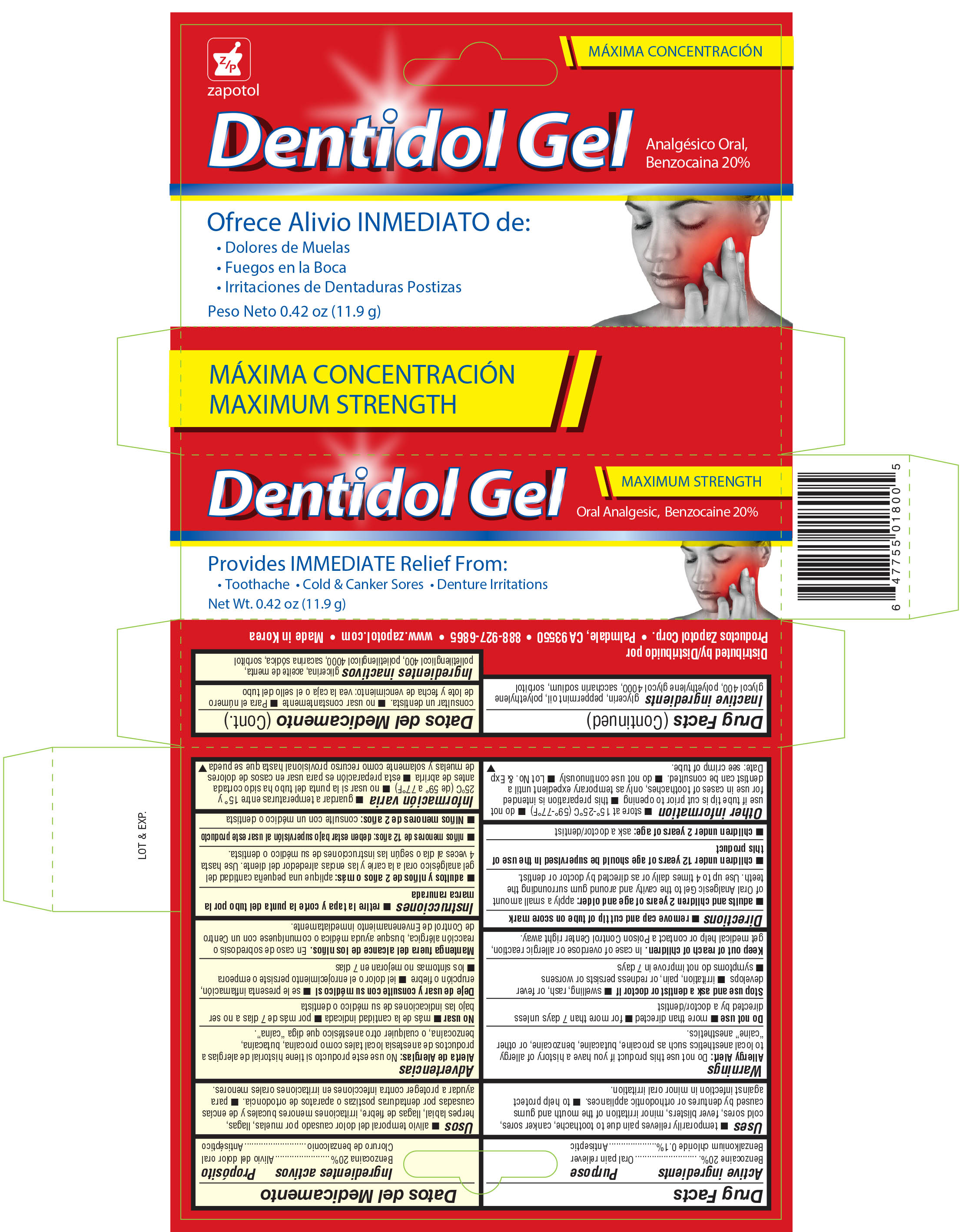 DRUG LABEL: Zapotol Dentidol Oral Analgesic
NDC: 59428-500 | Form: GEL
Manufacturer: Productos Zapotol Corp.
Category: otc | Type: HUMAN OTC DRUG LABEL
Date: 20161101

ACTIVE INGREDIENTS: BENZOCAINE 20 g/100 g; BENZALKONIUM CHLORIDE .1 g/100 g
INACTIVE INGREDIENTS: GLYCERIN; PEPPERMINT OIL; POLYETHYLENE GLYCOL 400; POLYETHYLENE GLYCOL 4000; SACCHARIN SODIUM; SORBITOL

Active ingredients Purpose

Benzocaine 20%.................................................................. Oral pain reliever

Benzalkonium chloride 0.1%................................................. Antiseptic

Uses

- temporarily relieves pain due to toothache, canker sores, cold sores, fever blisters, minor irritation of the mouth and gums caused by dentures or orthodontic appliances.
- to help protect against infection in minor oral irritation.

Warnings

Allergy Alert: Do not use this product if you have a history of allergy to local anesthetics such as procaine, butacaine, benzocaine, or other "caine" anesthetics.

Do not use

- more than directed
- for more than 7 days unless directed by a doctor/dentist

Stop use and ask a dentist or doctor if

- swelling, rash, or fever develops
- irritation, pain, or redness persists or worsens
- symptoms do not improve in 7 days

Keep out of reach of children. In case of overdose or allergic reaction, get medical help or contact a Poison Control Center right away.

Directions

- remove cap and cut tip of tube on score mark
- adults and children 2 years of age and older: apply a small amount of Oral Analgesic Gel to the cavity and around gum surrounding the teeth. Use up to 4 times daily or as directed by doctor or dentist.
- children under 12 years of age should be supervised in the use of this product
- children under 2 years of age: ask a doctor/dentist

Other information

- store at 15°-25°C (59°-77°F)
- do not use if tube tip is cut prior to opening
- this preparation is intended for use in cases of toothaches, only as temporary expedient until a dentist can be consulted.
- do not use continuously
- Lot No. & Exp Date: see crimp of tube.

Inactive ingredients

glycerin, peppermint oil, polyethylene glycol 400, polyethylene glycol 4000, saccharin sodium, sorbitol

DOSAGE AND ADMINISTRATION

Distributed by:

Productos Zapotol Corp.

Palmdale, CA 93550

Made in Korea